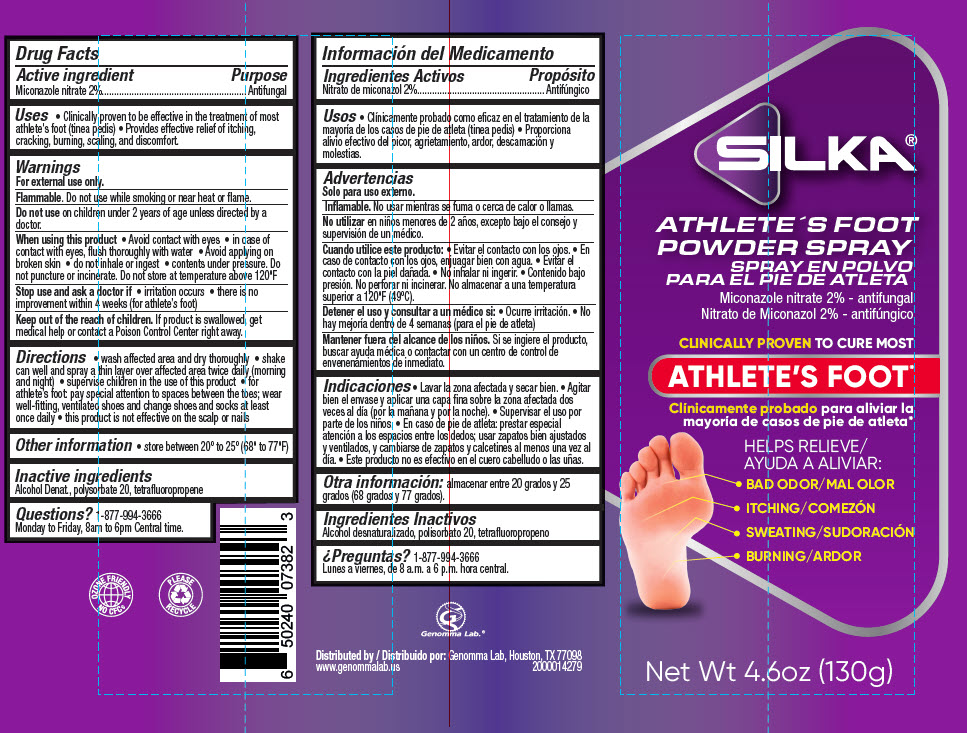 DRUG LABEL: Silka Athletes Foot
NDC: 50066-084 | Form: AEROSOL, SPRAY
Manufacturer: Genomma Lab USA
Category: otc | Type: HUMAN OTC DRUG LABEL
Date: 20250205

ACTIVE INGREDIENTS: MICONAZOLE NITRATE 20 mg/1 g
INACTIVE INGREDIENTS: POLYSORBATE 20; ALCOHOL; 1-CHLORO-3,3,3-TRIFLUOROPROPENE

Silka® Athlete's Foot Spray

Drug Facts

Active ingredient

Miconazole nitrate 2%

Purpose

Antifungal

Uses

- Clinically proven to be effective in the treatment of most athlete's foot (tinea pedis)
- Provides effective relief of itching, cracking, burning, scaling, and discomfort.

Warnings

For external use only.

Flammable. Do not use while smoking or near heat or flame.

Do not use on children under 2 years of age unless directed by a doctor.

When using this product

- Avoid contact with eyes
- in case of contact with eyes, flush thoroughly with water
- Avoid applying on broken skin
- do not inhale or ingest
- contents under pressure. Do not puncture or incinerate. Do not store at temperature above 120°F

Stop use and ask a doctor if

- irritation occurs
- there is no improvement within 4 weeks (for athlete's foot)

KEEP OUT OF REACH OF CHILDREN

Keep out of the reach of children. If product is swallowed, get medical help or contact a Poison Control Center right away.

Directions

- wash affected area and dry thoroughly
- shake can well and spray a thin layer over affected area twice daily (morning and night)
- supervise children in the use of this product
- for athlete's foot: pay special attention to spaces between the toes; wear well-fitting, ventilated shoes and change shoes and socks at least once daily
- this product is not effective on the scalp or nails

Other information

- store between 20° to 25° (68° to 77°F)

Inactive ingredients

Alcohol Denat., polysorbate 20, tetrafluoropropene

Questions?

1-877-994-3666 Monday to Friday, 8am to 6pm Central time.

Distributed by: Genomma Lab, Houston, TX 77098

PRINCIPAL DISPLAY PANEL - 130 g Canister Label

SILKA®
ATHLETE'S FOOT
POWDER SPRAY

Miconazole nitrate 2% - antifungal

CLINICALLY PROVEN TO CURE MOST
ATHLETE'S FOOT*

HELPS RELIEVE

- BAD ODOR
- ITCHING
- SWEATING
- BURNING

Net Wt 4.6oz (130g)